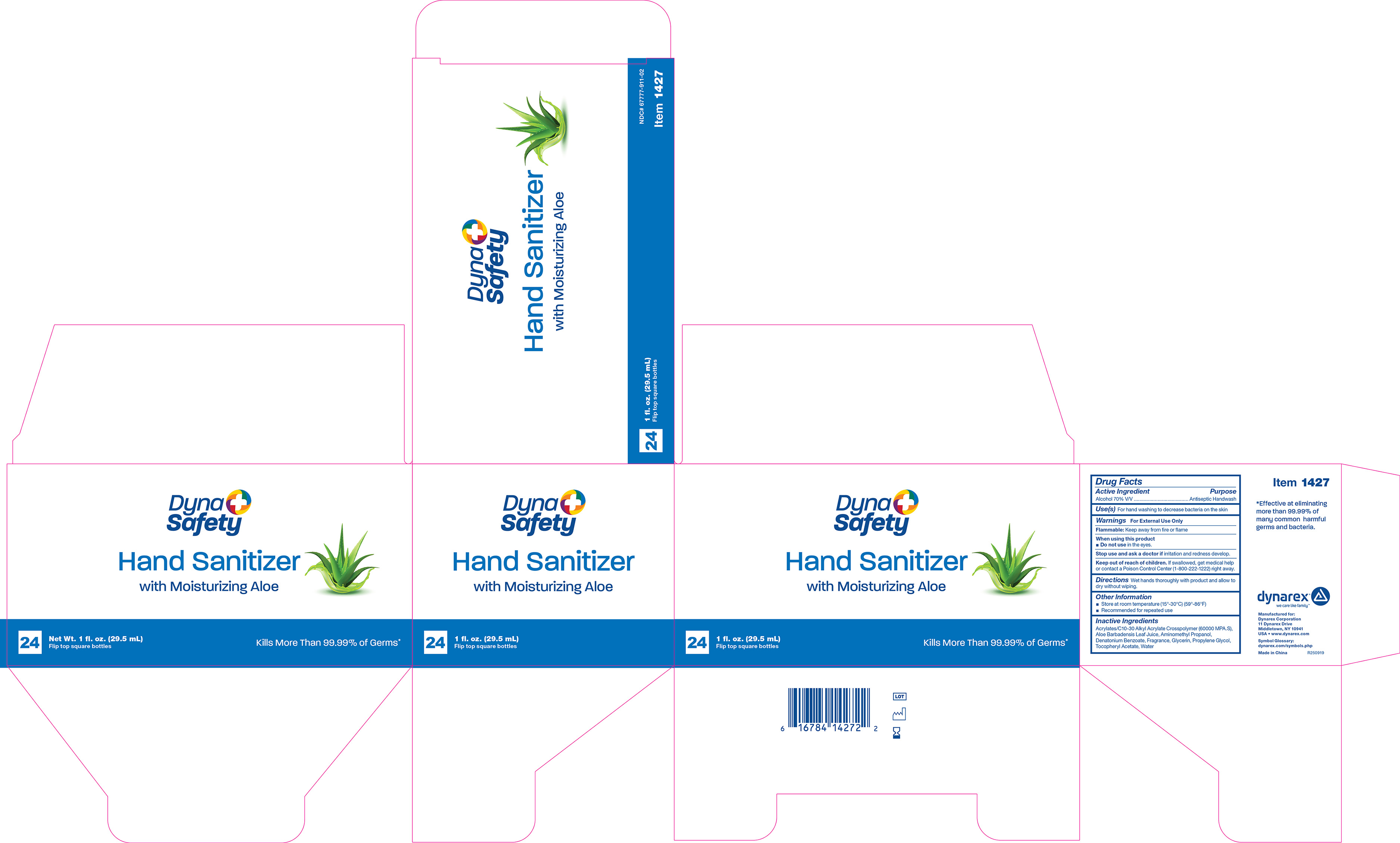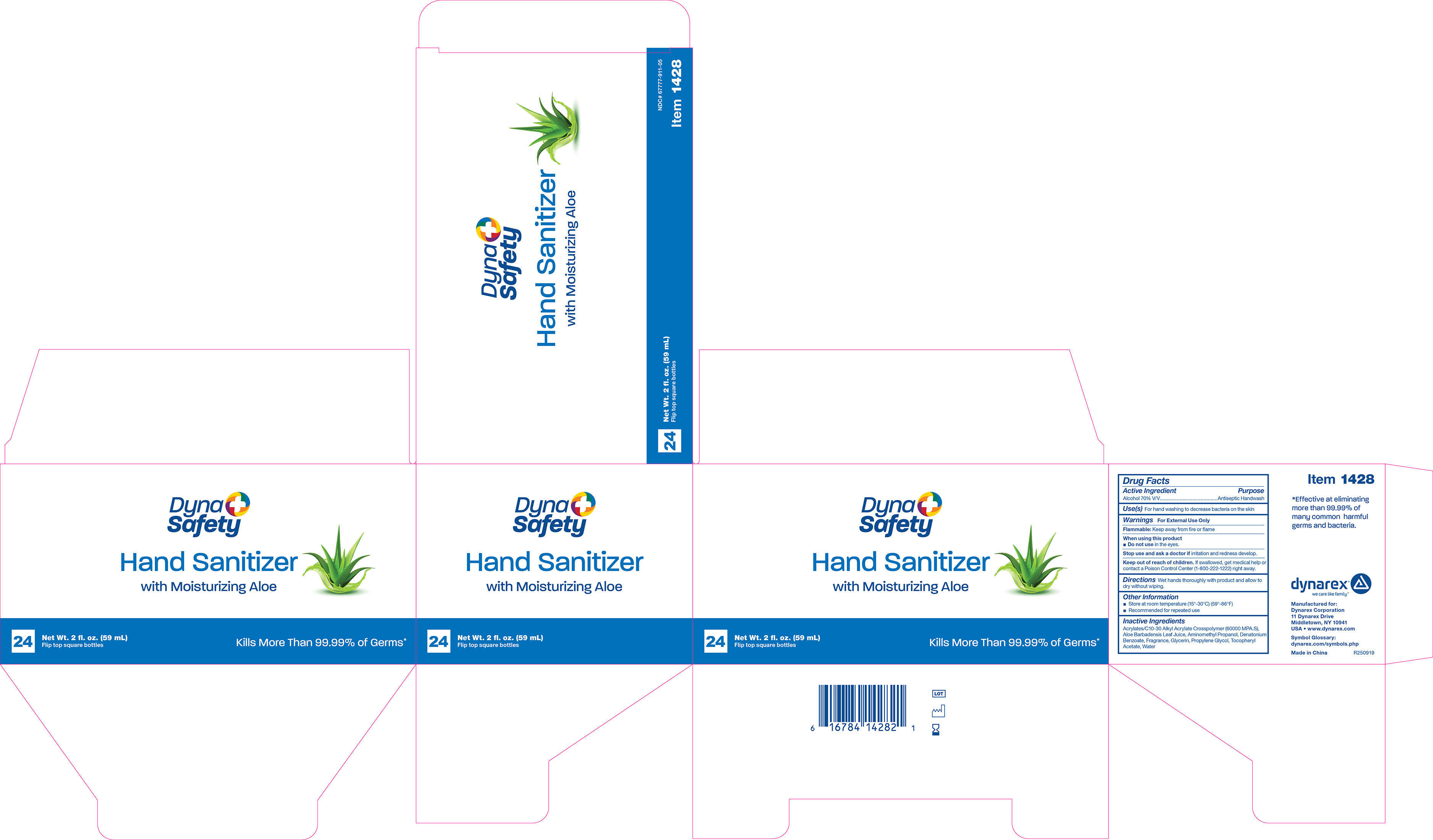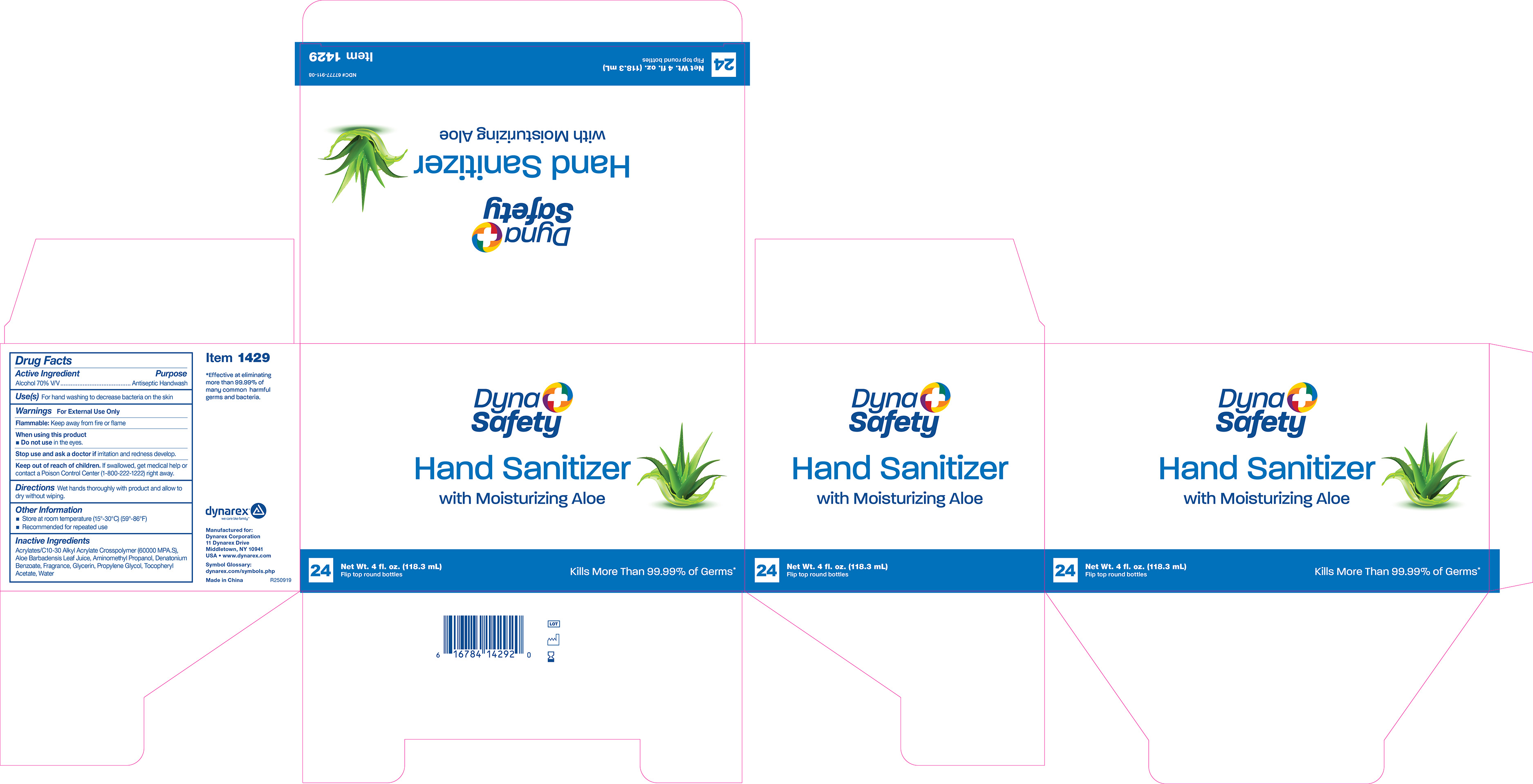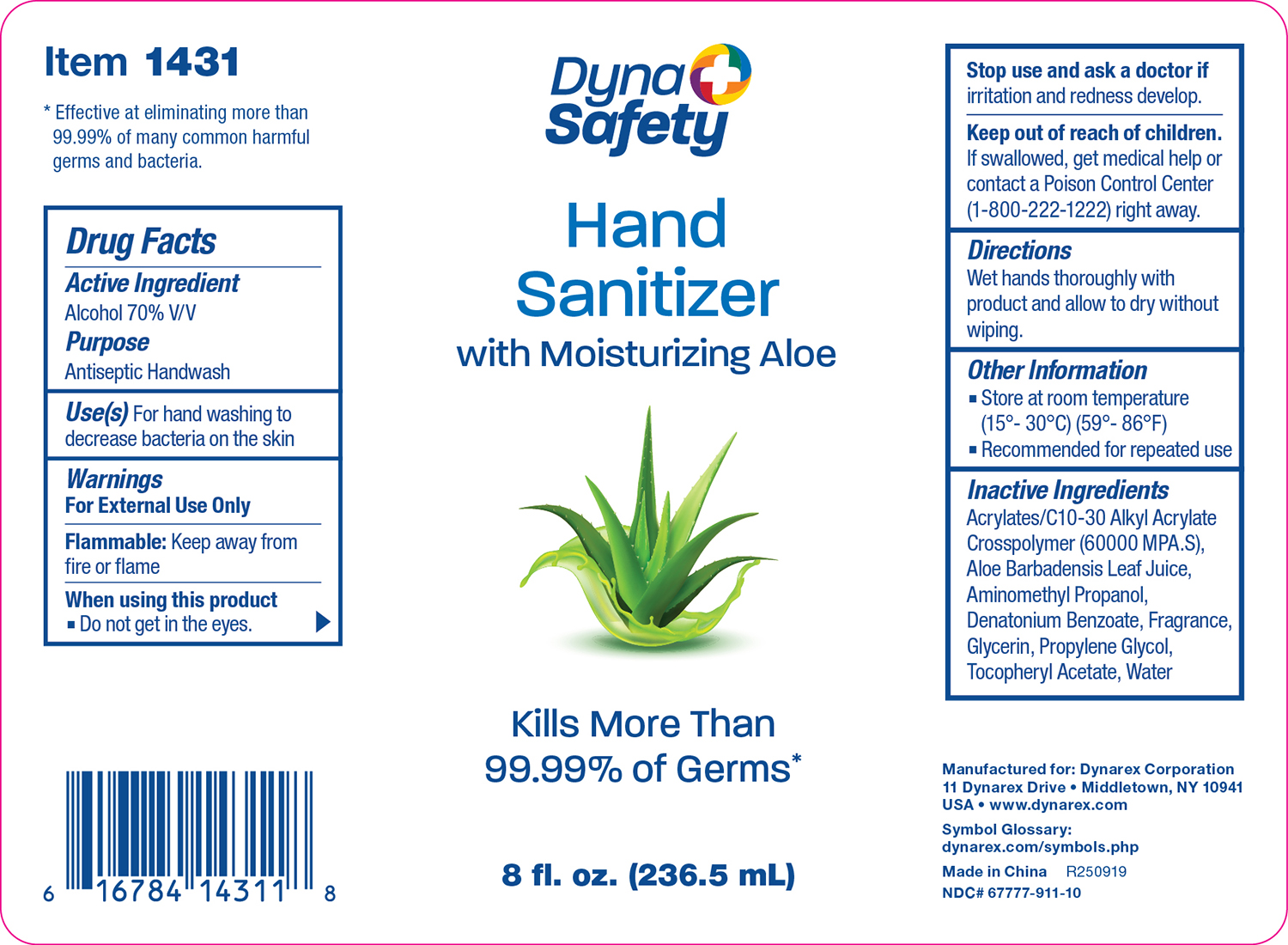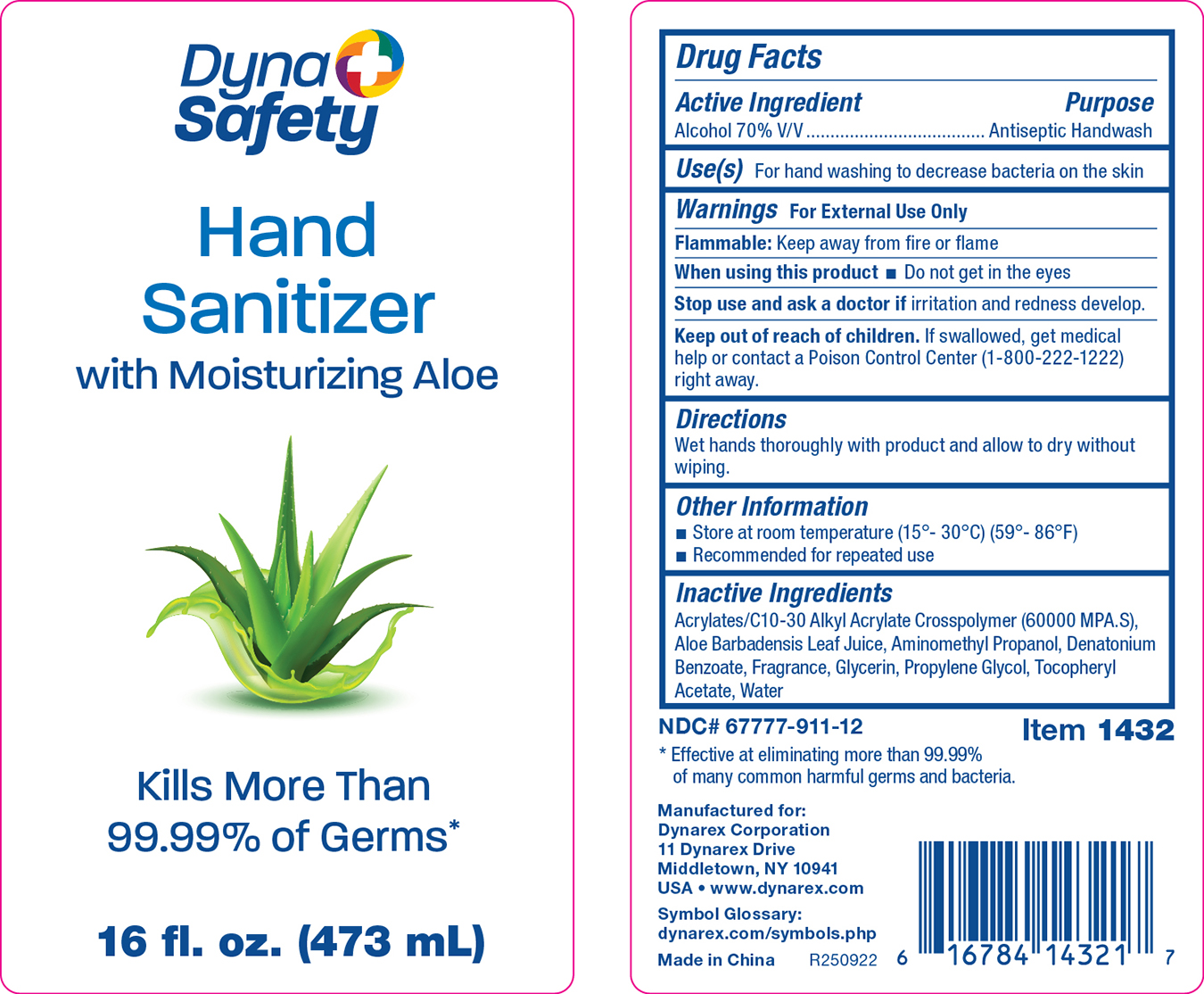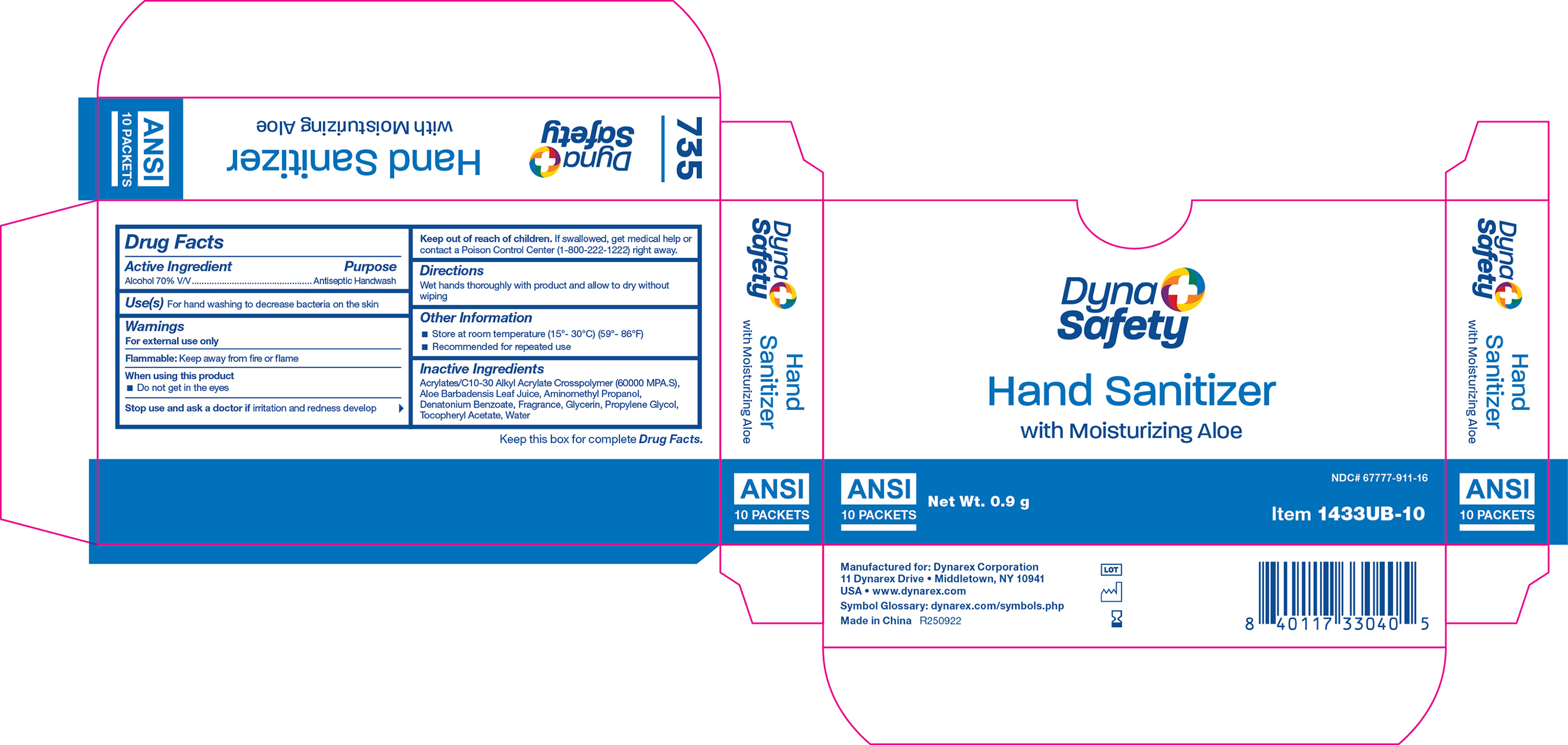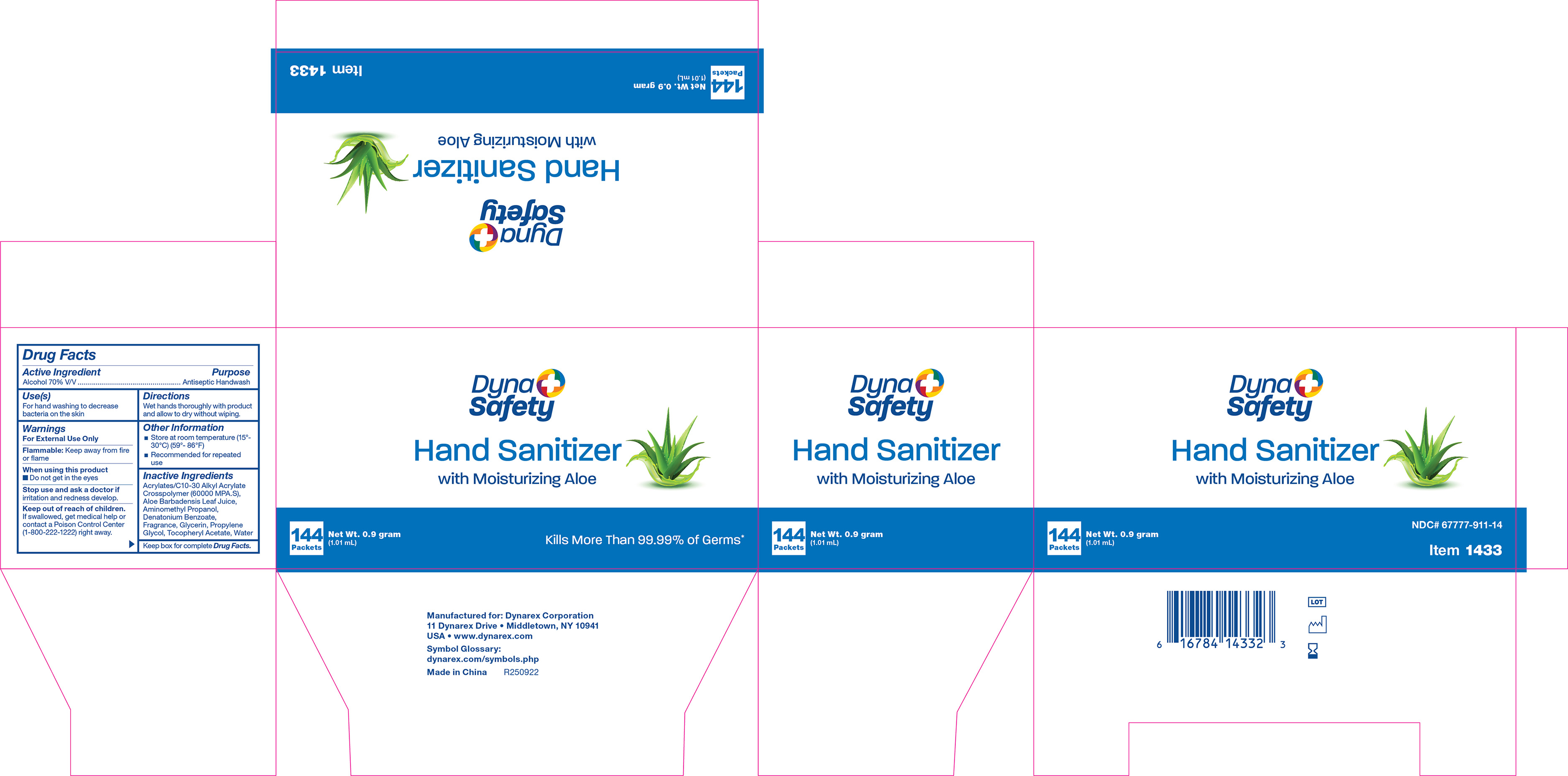 DRUG LABEL: Hand Sanitizer
NDC: 67777-911 | Form: GEL
Manufacturer: Dynarex Corporation
Category: otc | Type: HUMAN OTC DRUG LABEL
Date: 20251203

ACTIVE INGREDIENTS: ALCOHOL 95% 70 mL/100 mL
INACTIVE INGREDIENTS: WATER; ALOE BARBADENSIS LEAF; DENATONIUM BENZOATE; ACRYLATES/C10-30 ALKYL ACRYLATE CROSSPOLYMER (60000 MPA.S); AMINOMETHYL PROPANOL; GLYCERIN; PROPYLENE GLYCOL; .ALPHA.-TOCOPHEROL ACETATE

1427 Hand Sanitizer
1428 Hand Sanitizer
1429 Hand Sanitizer
1431 Hand Sanitizer
1432 Hand Sanitizer
1433 Hand Sanitizer
1433UB-10 Hand Sanitizer

Active ingredient

Alcohol 70% V/V

Purpose

Antiseptic Handwash

Use

For hand washing to decrease bacteria on the skin

Warnings

For external use only

Flammable: Keep away from fire or flame

When using this product

• Do not get in the eyes

Stop use and ask a doctor if

irritation and redness develop

Keep out of reach of children.

If swallowed, get medical help or contact a Poison Control Center (1-800-222-1222) right away.

Directions

Wet hands thoroughly with product and allow to dry without wiping

Other information

• Store at room temperature (15º - 30ºC) (59º - 86ºF)

• Recommended for repeated use

Inactive ingredients

acrylates/C10-30 alkyl acrylate crosspolymer (60000 MPA.S), aloe barbadensis leaf juice, aminomethyl propanol, denatonium benzoate, fragrance, glycerin, propylene glycol, tocopheryl acetate, water

Label

1427 Label

Label

1428 Label

Label

1429 Label

Label

1431 Label

Label

1432 Label

Label

1433 Label

Label

1433UB-10 Label